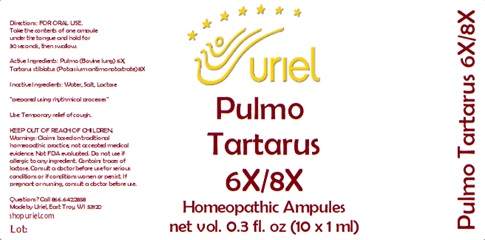 DRUG LABEL: Pulmo Tartarus 6/8
NDC: 48951-8092 | Form: LIQUID
Manufacturer: Uriel Pharmacy Inc.
Category: homeopathic | Type: HUMAN OTC DRUG LABEL
Date: 20240112

ACTIVE INGREDIENTS: SUS SCROFA LUNG 6 [hp_X]/1 mL; ANTIMONY POTASSIUM TARTRATE 8 [hp_X]/1 mL
INACTIVE INGREDIENTS: WATER; SODIUM CHLORIDE; LACTOSE

Pulmo Tartarus 6/8

INDICATIONS AND USAGE

Directions: FOR ORAL USE.

DOSAGE AND ADMINISTRATION

Take the contents of one ampule under the tongue and hold for 30 seconds, then swallow.

ACTIVE INGREDIENT

Active Ingredients: Pulmo (Bovine lung) 6X, Tartarus stibiatus (Potassium antimonotartrate) 8X

Inactive Ingredients: Water, Salt, Lactose

"prepared using rhythmical processes"

PURPOSE

Use: Temporary relief of cough.

KEEP OUT OF REACH OF CHILDREN.

WARNINGS

Warnings: Claims based on traditional homeopathic practice, not accepted medical evidence. Not FDA evaluated. Do not use if allergic to any ingredient. Contains traces of lactose. Consult a doctor before use for serious conditions or if conditions worsen or persist. If pregnant or nursing, consult a doctor before use.

QUESTIONS

Questions? Call 866.642.2858 Made by Uriel, East Troy, WI 53120 shopuriel.com